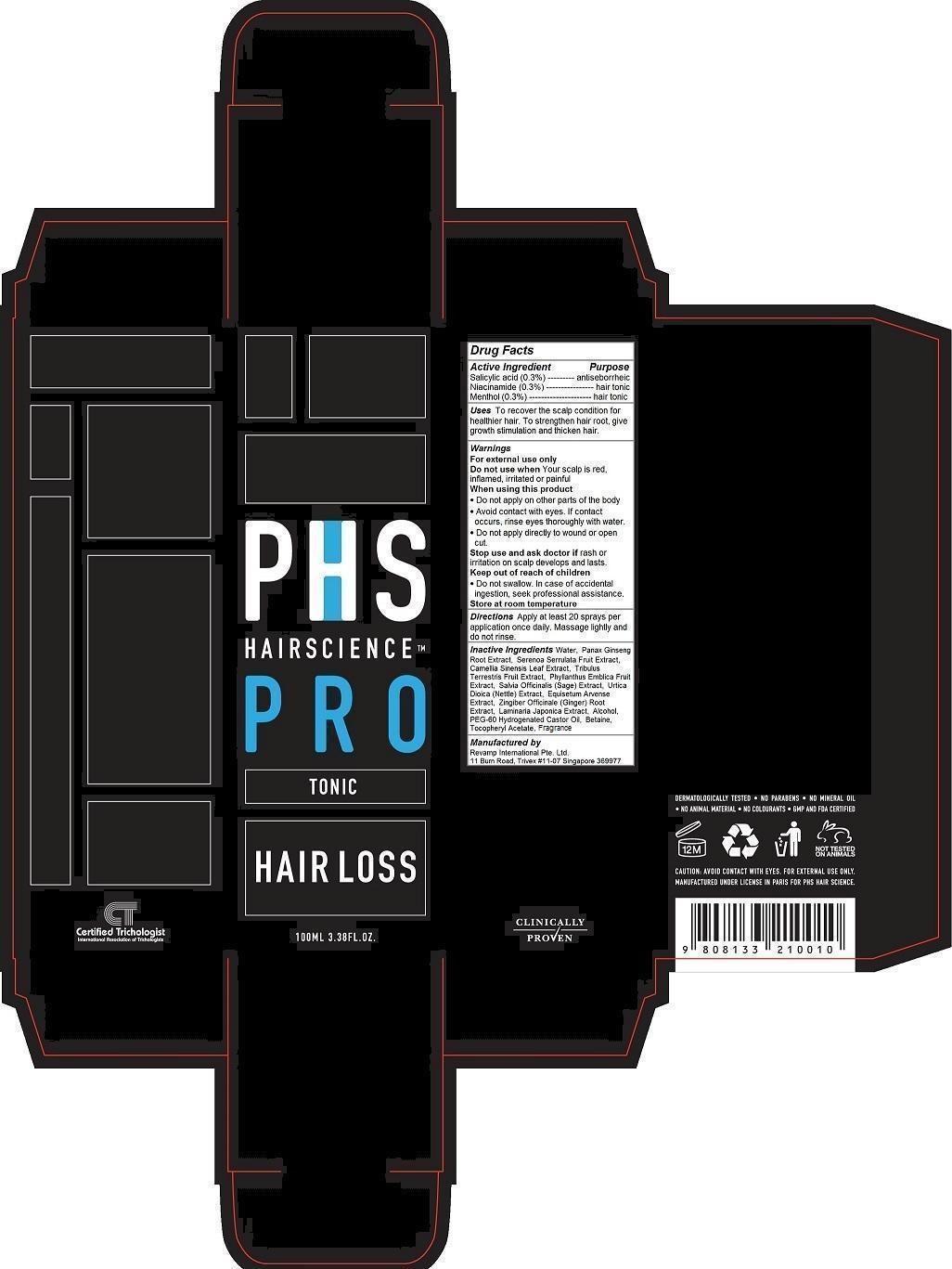 DRUG LABEL: PHS Hair Science Pro Hair Loss Tonic
NDC: 69149-100 | Form: LIQUID
Manufacturer: Revamp International Pte. Ltd.
Category: otc | Type: HUMAN OTC DRUG LABEL
Date: 20140919

ACTIVE INGREDIENTS: SALICYLIC ACID 0.3 1/100 mL; NIACINAMIDE 0.3 1/100 mL; MENTHOL 0.3 1/100 mL
INACTIVE INGREDIENTS: WATER; ASIAN GINSENG; SAW PALMETTO; GREEN TEA LEAF; TRIBULUS TERRESTRIS FRUIT; PHYLLANTHUS EMBLICA FRUIT; SALVIA OFFICINALIS WHOLE; URTICA DIOICA LEAF; EQUISETUM ARVENSE BRANCH; GINGER; LAMINARIA JAPONICA; ALCOHOL; PEG-60 HYDROGENATED CASTOR OIL; BETAINE; .ALPHA.-TOCOPHEROL ACETATE

PHS Hair Science Pro Hair Loss Tonic